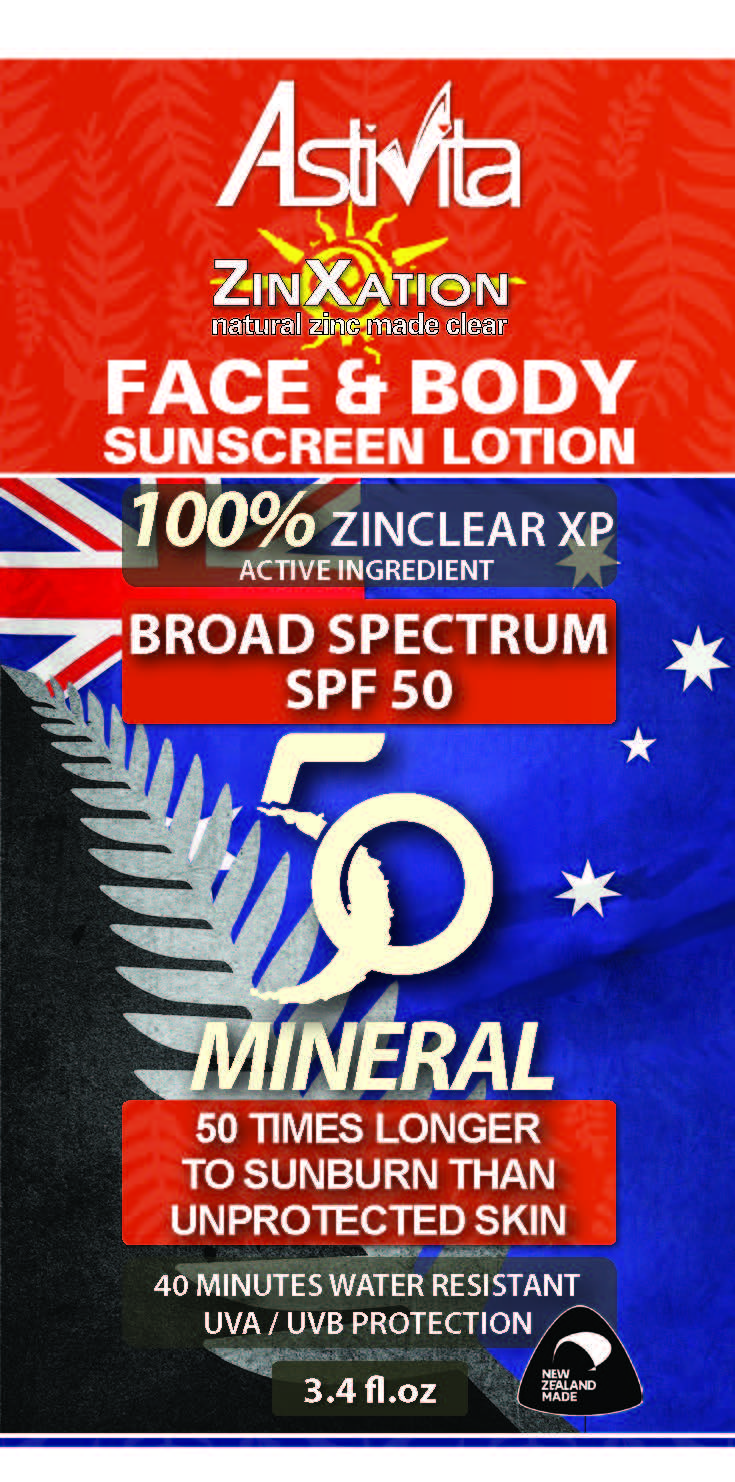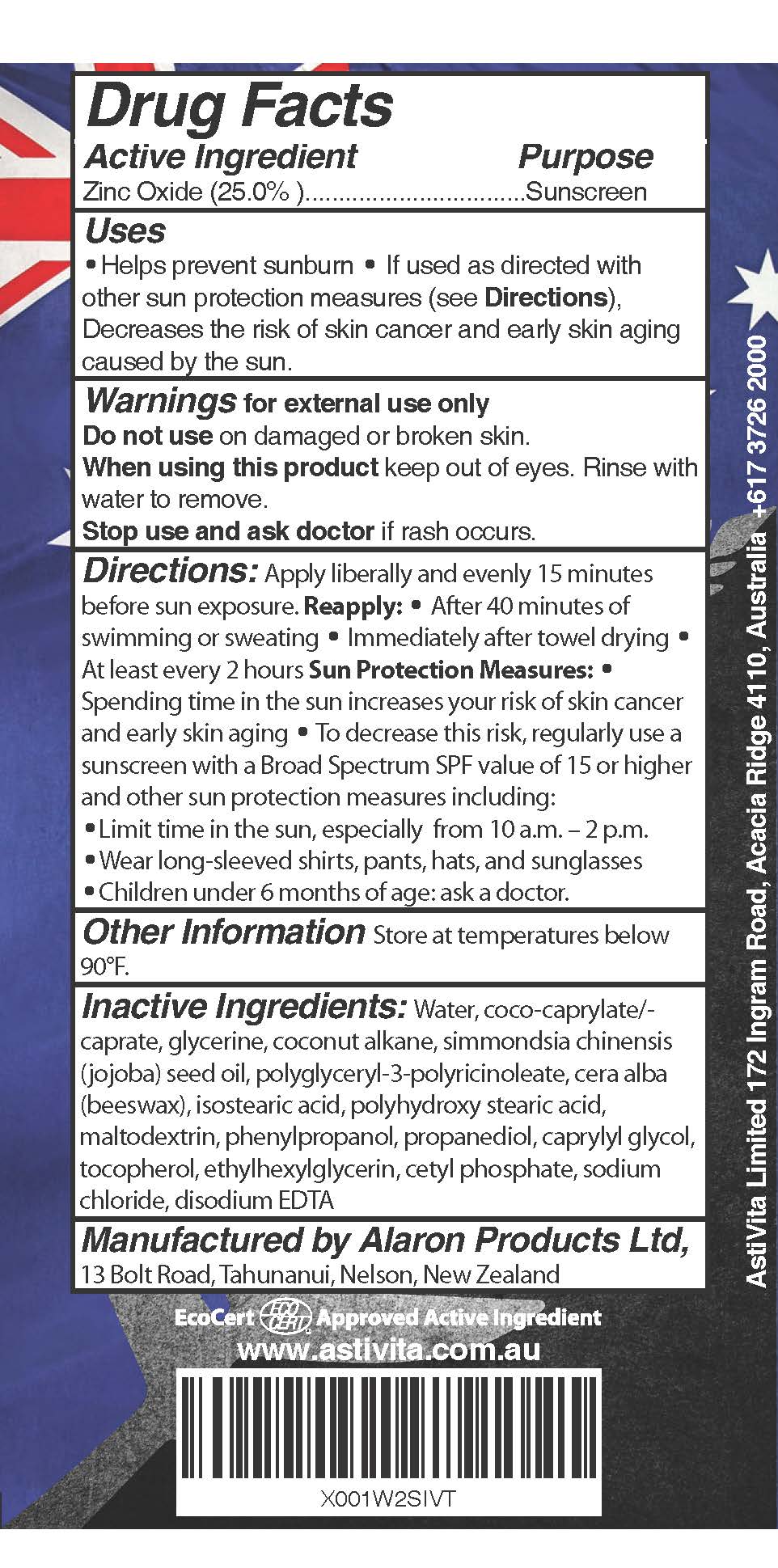 DRUG LABEL: ZINXATION SUNSCREEN
NDC: 80982-001 | Form: LOTION
Manufacturer: ASTIVITA LIMITED
Category: otc | Type: HUMAN OTC DRUG LABEL
Date: 20210729

ACTIVE INGREDIENTS: ZINC OXIDE 25 g/100 g
INACTIVE INGREDIENTS: COCO-CAPRYLATE/CAPRATE; GLYCERIN; COCONUT ALKANES; JOJOBA OIL; POLYGLYCERYL-3 RICINOLEATE; YELLOW WAX; ISOSTEARIC ACID; POLYHYDROXYSTEARIC ACID (2300 MW); MALTODEXTRIN; PHENYLPROPANOL; PROPANEDIOL; CAPRYLYL GLYCOL; TOCOPHEROL; ETHYLHEXYLGLYCERIN; CETYL PHOSPHATE; SODIUM CHLORIDE; EDETATE DISODIUM

ZINXATION SUNSCREEN LOTION SPF-50

ACTIVE INGREDIENT

ZINC OXIDE 25%

PURPOSE

SUNSCREEN

USES

- Helps prevent sunburn
- If used as directed with other sun protection measures (see Directions), decreased the risk of skin cancer and early skin aging caused by the sun

WARNINGS

- Avoid prolonged exposure in the sun.
- Wear protective clothing-hats and sunglasses.
- Do not swallow.
- For external use only.
- Avoid contact with eyes.
- If a rash or irritation occurs discontinue use.

DIRECTIONS:

- Apply generously to all areas 20 minutes before sun exposure.
- Reapply every 2 hours or after swimming.

INACTIVE INGREDIENTS

Coco-caprylate/caprate, glycerine, coconut alkane, simmondsia chinensis (jojoba) seed oil, polyglyceryl-3-polyricinoleate, cera alba (beeswax), isostearic acid, polyhydroxy stearic acid, maltodextrin, phenylpropanol, propanediol, caprylyl glycol, tocopherol, ethylhexylglycerin, cetyl phosphate, sodium chloride, disodium EDTA

QUESTIONS OR COMMENTS?

Call +61 73726 2030